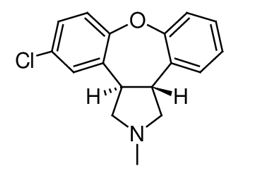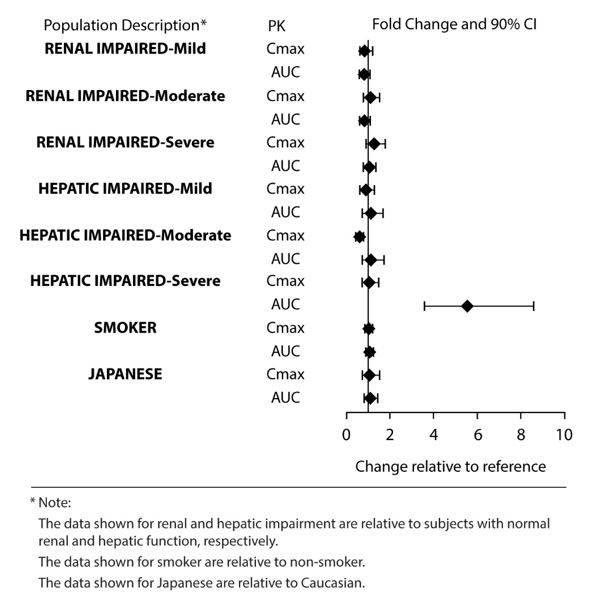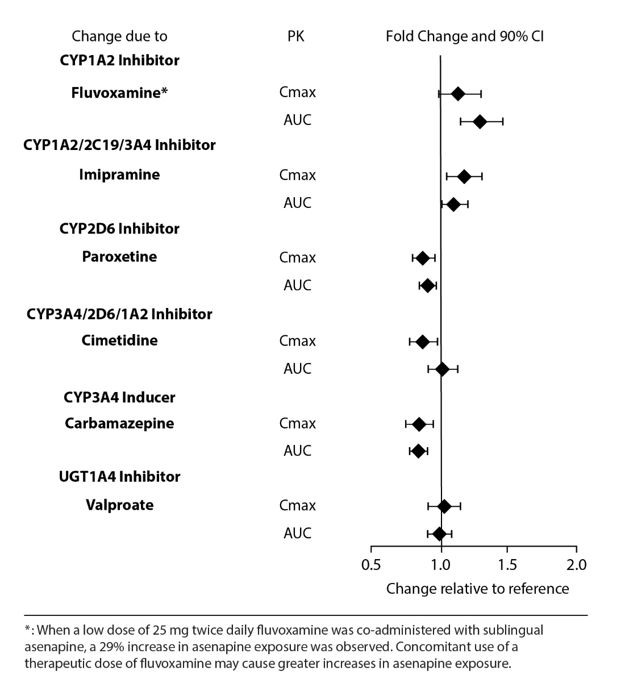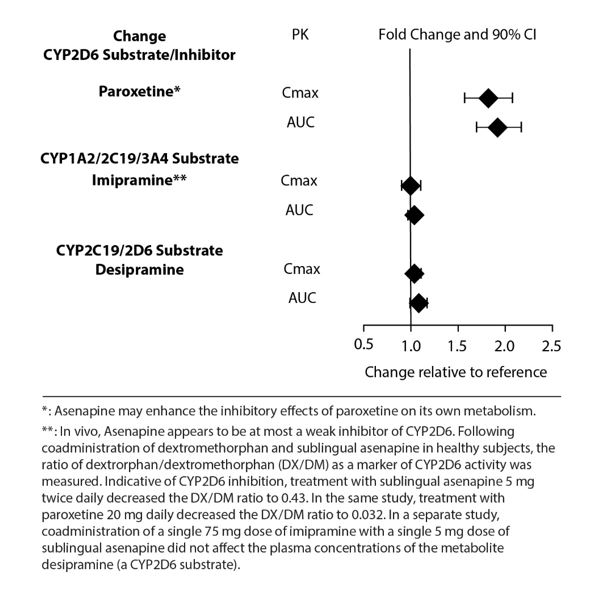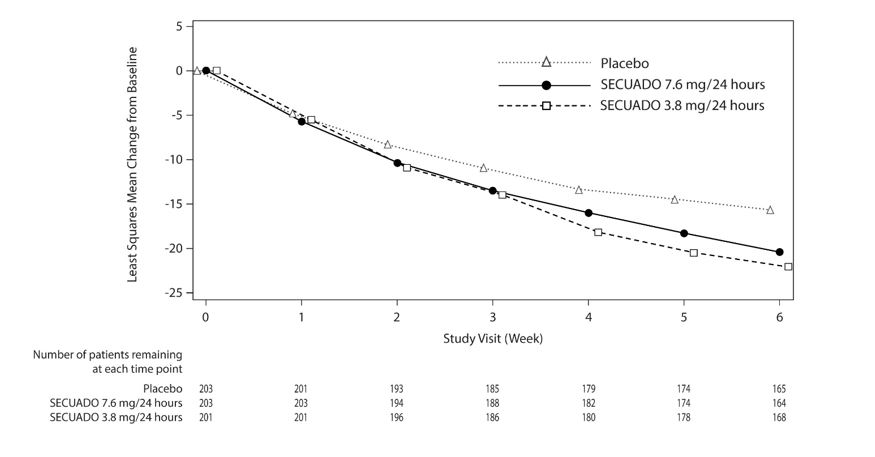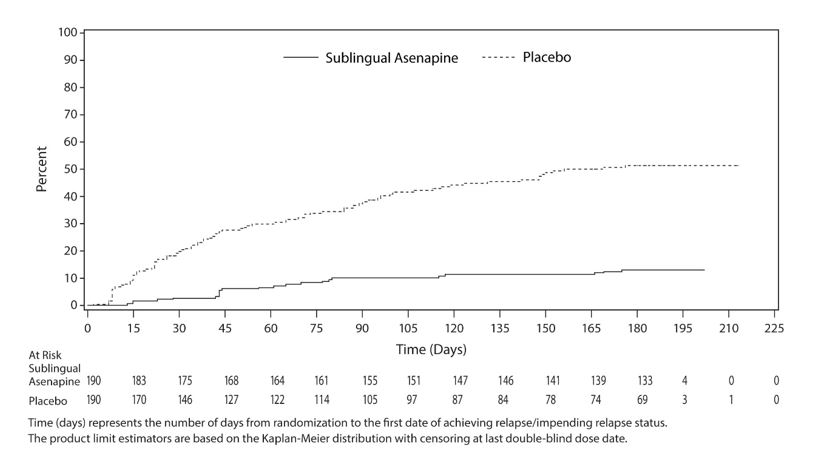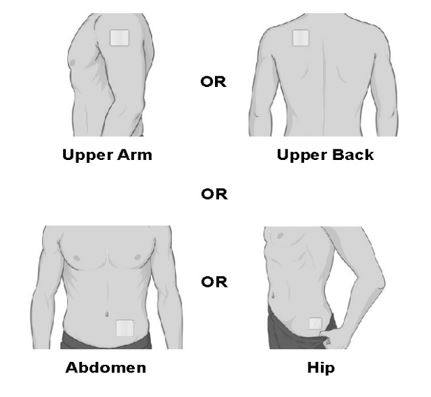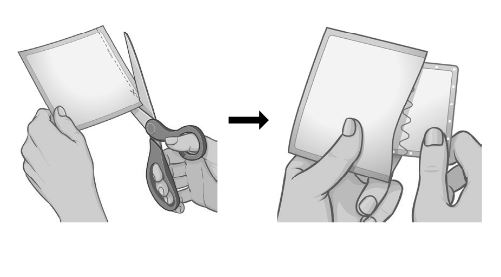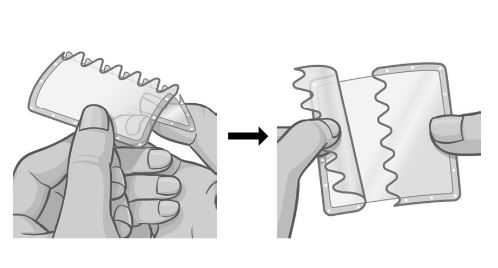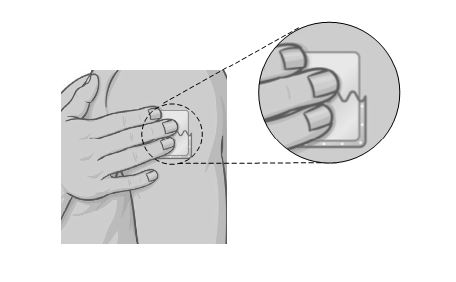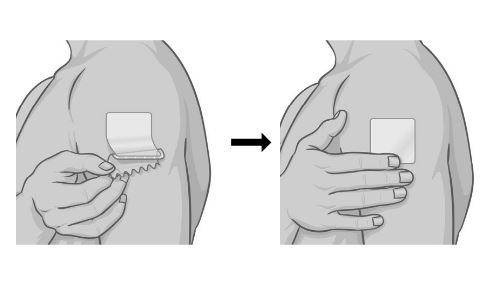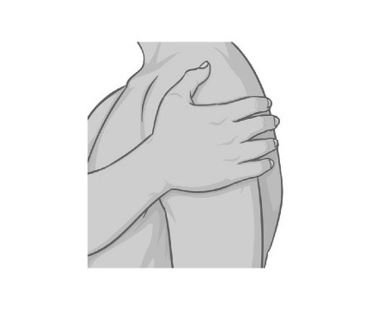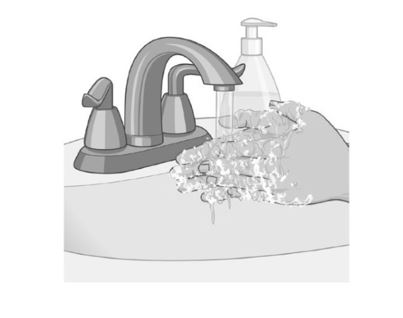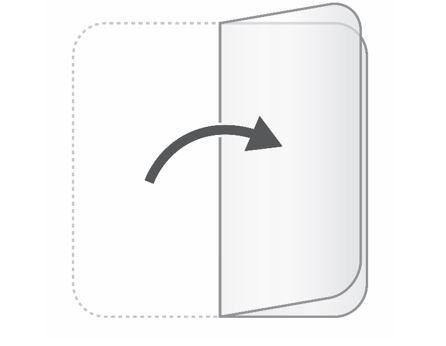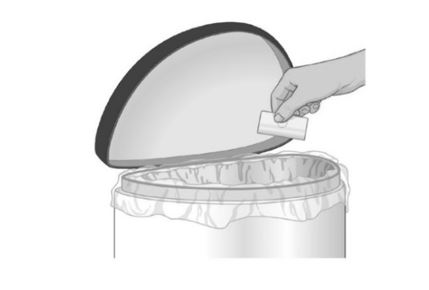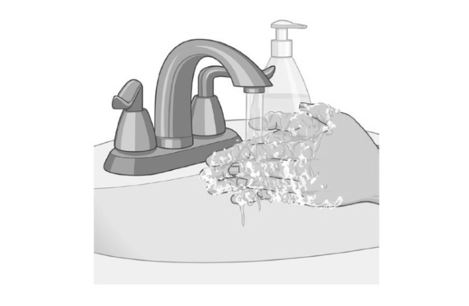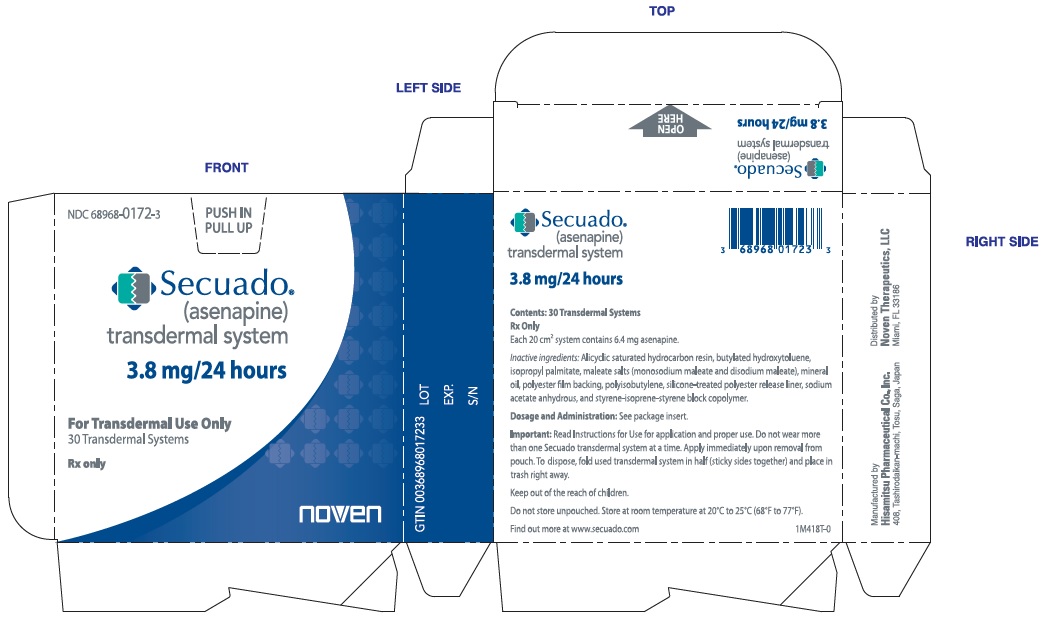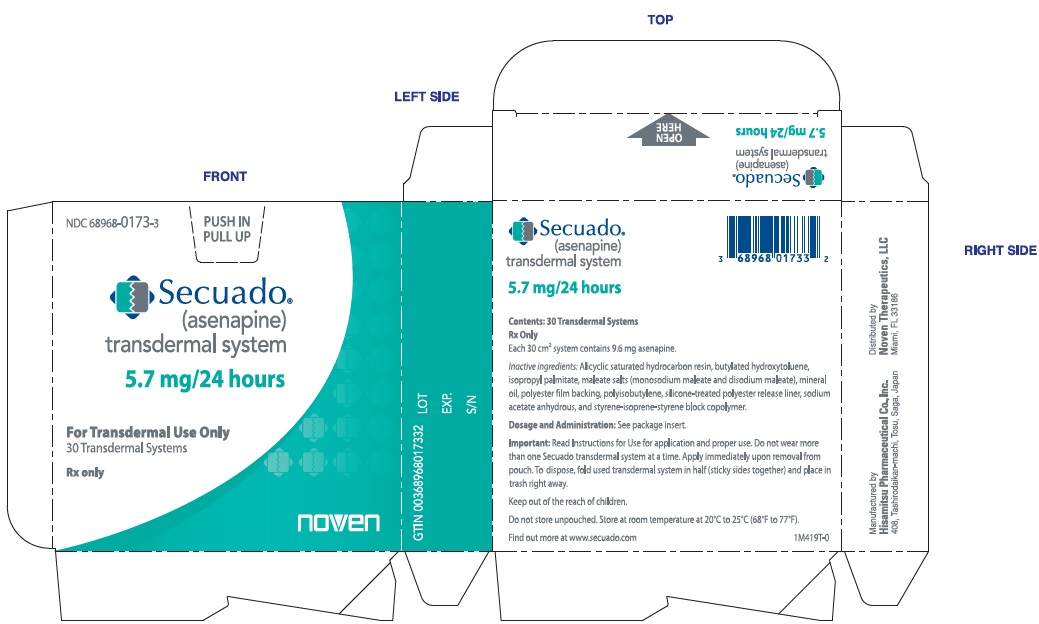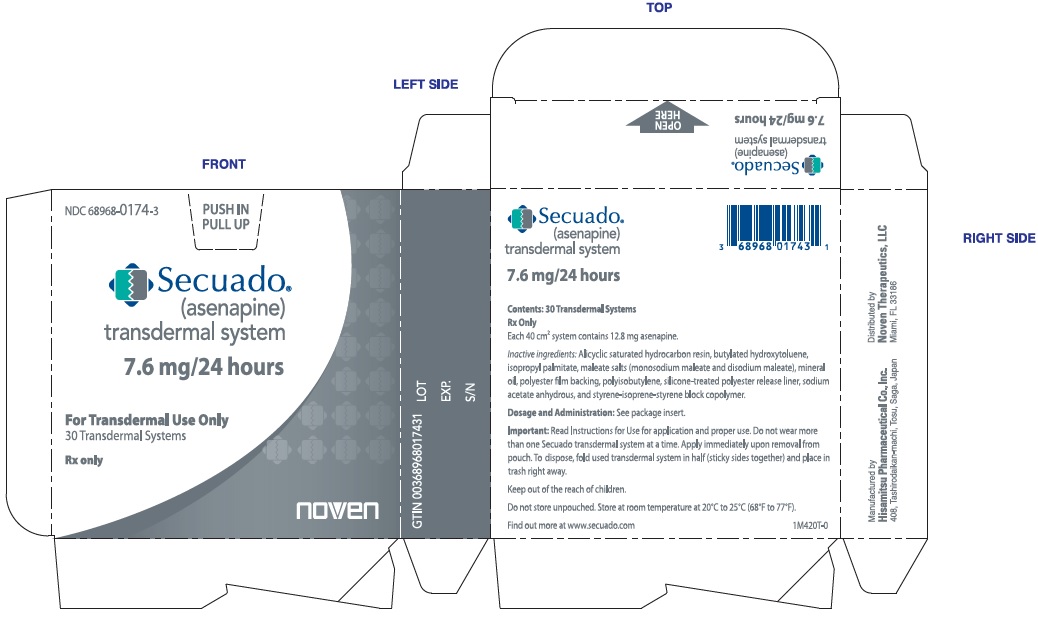 DRUG LABEL: SECUADO
NDC: 68968-0172 | Form: FILM, EXTENDED RELEASE
Manufacturer: Noven Therapeutics, LLC
Category: prescription | Type: HUMAN PRESCRIPTION DRUG LABEL
Date: 20250130

ACTIVE INGREDIENTS: ASENAPINE 3.8 mg/1 d
INACTIVE INGREDIENTS: POLYISOBUTYLENE (1100000 MW); MINERAL OIL; SODIUM ACETATE ANHYDROUS; ISOPROPYL PALMITATE; BUTYLATED HYDROXYTOLUENE

HIGHLIGHTS OF PRESCRIBING INFORMATION

These highlights do not include all the information needed to use SECUADO® (asenapine) transdermal system safely and effectively. See full prescribing information for SECUADO®.
SECUADO® (asenapine) transdermal system
Initial U.S. Approval: 2009

WARNING: INCREASED MORTALITY IN ELDERLY PATIENTS WITH DEMENTIA-RELATED PSYCHOSIS

See full prescribing information for complete boxed warning.
Elderly patients with dementia-related psychosis treated with antipsychotic drugs are at an increased risk of death. SECUADO is not approved for the treatment of patients with dementia-related psychosis. (5.1)

RECENT MAJOR CHANGES

WARNINGS AND PRECAUTIONS (5.11) | 1/2025

1 INDICATIONS AND USAGE

SECUADO is an atypical antipsychotic indicated for the treatment of adults with schizophrenia. (1)

2 DOSAGE AND ADMINISTRATION

- For transdermal use only. (2.2)
- Apply one SECUADO transdermal system every 24 hours. (2.2)
- Apply SECUADO to one of the following sites: the hip, abdomen, upper arm, or upper back area. (2.2)
- The recommended starting dose of SECUADO is 3.8 mg/24 hours. May increase dosage to 5.7 mg/24 hours or 7.6 mg/24 hours after one week. (2.1)

3 DOSAGE FORMS AND STRENGTHS

- Transdermal System: 3.8 mg/24 hours, 5.7 mg/24 hours and 7.6 mg/24 hours (3)

4 CONTRAINDICATIONS

- Severe hepatic impairment (Child-Pugh C). (8.7, 12.3)
- Known hypersensitivity to SECUADO or to any components in the transdermal system. (4, 5.6, 17)

5 WARNINGS AND PRECAUTIONS

- Cerebrovascular Adverse Reactions in Elderly Patients with Dementia-Related Psychosis: Increased incidence of cerebrovascular adverse reactions (e.g., stroke, transient ischemic attack). (5.2)
- Neuroleptic Malignant Syndrome: Manage with immediate discontinuation and close monitoring. (5.3)
- Tardive Dyskinesia: Discontinue if clinically appropriate. (5.4)
- Metabolic Changes: Monitor for hyperglycemia/diabetes mellitus, dyslipidemia, and weight gain. (5.5)
- Orthostatic Hypotension: Monitor heart rate and blood pressure and warn patients with known cardiovascular or cerebrovascular disease, and risk of dehydration or syncope. (5.7)
- Leukopenia, Neutropenia, and Agranulocytosis: Perform complete blood counts (CBC) in patients with pre-existing low white blood cell count (WBC) or history of leukopenia or neutropenia. Consider discontinuing SECUADO if a clinically significant decline in WBC occurs in absence of other causative factors. (5.9)
- QT Prolongation: Increases in QT interval; avoid use with drugs that also increase the QT interval and in patients with risk factors for prolonged QT interval. (5.10)
- Seizures: Use cautiously in patients with a history of seizures or with conditions that lower the seizure threshold. (5.12)
- Potential for Cognitive and Motor Impairment: Use caution when operating machinery. (5.13)
- External Heat: Avoid exposing SECUADO to external heat sources during wear because both the rate and extent of absorption are increased. (5.16)
- Application Site Reactions: During wear time or immediately after removal of SECUADO, local skin reactions may occur. Instruct patients to select a different transdermal system application site each day to limit the occurrence of skin reactions. (5.17)

6 ADVERSE REACTIONS

Commonly observed adverse reactions (incidence ≥5% and at least twice that for placebo): Extrapyramidal disorder, application site reaction, and weight gain.(6.1)

To report SUSPECTED ADVERSE REACTIONS, contact Noven Therapeutics, LLC at 1-800-455-8070 or FDA at 1-800-FDA-1088 or www.fda.gov/medwatch.

7 DRUG INTERACTIONS

- Antihypertensive drugs: SECUADO may enhance antihypertensive effects. Monitor blood pressure and adjust dosage of antihypertensive drug accordingly. (7.1)
- Strong CYP1A2 Inhibitors: Consider dose reduction for SECUADO based on clinical response. (7.1)
- Paroxetine (CYP2D6 substrate and inhibitor): Reduce paroxetine dose by half. (7.1)

8 USE IN SPECIFIC POPULATIONS

Pregnancy: May cause extrapyramidal and/or withdrawal symptoms in neonates with third trimester exposure. (8.1)

FULL PRESCRIBING INFORMATION

WARNING: INCREASED MORTALITY IN ELDERLY PATIENTS WITH DEMENTIA-RELATED PSYCHOSIS

Elderly patients with dementia-related psychosis treated with antipsychotic drugs are at an increased risk of death. SECUADO is not approved for the treatment of patients with dementia-related psychosis [see Warnings and Precautions (5.1)].

1 INDICATIONS AND USAGE

SECUADO is indicated for the treatment of adults with schizophrenia [see Clinical Studies (14)].

2 DOSAGE AND ADMINISTRATION

2.1 Schizophrenia

Initiate SECUADO at a dosage of 3.8 mg/24 hours. In a short-term, placebo-controlled trial, there was no suggestion of added benefit at a dosage of 7.6 mg/24 hours, on average, but there was an increase in certain adverse reactions. The dosage may be increased to 5.7 mg/24 hours or 7.6 mg/24 hours, as needed, after one week. The safety of doses above 7.6 mg/24 hours has not been evaluated in clinical studies [see Clinical Studies (14)].

Based on the average exposure (AUC) of asenapine, SECUADO 3.8 mg/24 hours corresponds to 5 mg twice daily of sublingual asenapine and SECUADO 7.6 mg/24 hours corresponds to 10 mg twice daily of sublingual asenapine [see Clinical Pharmacology (12.3)].

2.2 Important Application Instructions

- See the FDA-approved patient labeling (Instructions for Use).
- SECUADO transdermal system is applied once daily. Each SECUADO transdermal system should be worn for 24 hours only. Instruct patients to wear only one SECUADO transdermal system at any time.
- Apply SECUADO to clean, dry, and intact skin at the selected application site. Application sites include: the upper arm, upper back, abdomen, or hip. Apply the transdermal system to a different application site each time a new SECUADO transdermal system is applied.
- Do not cut open the pouch until ready to apply SECUADO and do not use the transdermal system if the individual pouch seal is broken or if it appears to be damaged. Do not cut SECUADO, the whole transdermal system should be applied.
- If the SECUADO transdermal system lifts at the edges, reattach SECUADO by pressing firmly and smoothing down the edges of the system. If SECUADO comes off completely, apply a new SECUADO transdermal system.
- Discard SECUADO by folding the used transdermal system so that the adhesive side sticks to itself and safely discard.
- If irritation or a burning sensation occurs while wearing SECUADO, remove the system and apply a new transdermal system to a new application site [see Warnings and Precautions (5.17)].
- Showering is permitted, but the use of SECUADO during swimming or taking a bath has not been evaluated.
- Do not apply external heat sources (e.g., heating pad) over the SECUADO transdermal system [see Warnings and Precautions (5.16)]. Prolonged application of heat over a SECUADO transdermal system increases plasma concentrations of asenapine [see Clinical Pharmacology (12.3)].

3 DOSAGE FORMS AND STRENGTHS

SECUADO (asenapine) transdermal system is a translucent rounded square product available in three dosage strengths:

- 3.8 mg asenapine / 24 hours
- 5.7 mg asenapine / 24 hours
- 7.6 mg asenapine / 24 hours

4 CONTRAINDICATIONS

SECUADO is contraindicated in patients with:

- Severe hepatic impairment (Child-Pugh C) [see Specific Populations (8.7), Clinical Pharmacology (12.3)].
- A history of hypersensitivity reactions to asenapine or any components of the transdermal system. Reactions with asenapine have included anaphylaxis, angioedema, hypotension, tachycardia, swollen tongue, dyspnea, wheezing and rash [see Warnings and Precautions (5.6), Adverse Reactions (6)].

5 WARNINGS AND PRECAUTIONS

5.1 Increased Mortality in Elderly Patients with Dementia-Related Psychosis

Elderly patients with dementia-related psychosis treated with antipsychotic drugs are at an increased risk of death. Analyses of 17 placebo-controlled trials (modal duration of 10 weeks), largely in patients taking atypical antipsychotic drugs, revealed a risk of death in the drug-treated patients of between 1.6 to 1.7 times that seen in placebo-treated patients. Over the course of a typical 10-week controlled trial, the rate of death in drug-treated patients was about 4.5%, compared to a rate of about 2.6% in the placebo group.

Although the causes of death were varied, most of the deaths appeared to be either cardiovascular (e.g., heart failure, sudden death) or infectious (e.g., pneumonia) in nature. SECUADO is not approved for the treatment of patients with dementia-related psychosis [see Warnings and Precautions (5.2)].

5.2 Cerebrovascular Adverse Reactions, Including Stroke, In Elderly Patients with Dementia-Related Psychosis

In placebo-controlled trials in elderly subjects with dementia, patients randomized to risperidone, aripiprazole, and olanzapine had a higher incidence of stroke and transient ischemic attack, including fatal stroke. SECUADO is not approved for the treatment of patients with dementia-related psychosis [see Warnings and Precautions (5.1)].

5.3 Neuroleptic Malignant Syndrome

A potentially fatal symptom complex sometimes referred to as Neuroleptic Malignant Syndrome (NMS) has been reported in association with administration of antipsychotic drugs. Clinical manifestations of NMS are hyperpyrexia, muscle rigidity, altered mental status, and evidence of autonomic instability. Additional signs may include elevated creatine phosphokinase, myoglobinuria (rhabdomyolysis), and acute renal failure.

If NMS is suspected, immediately discontinue SECUADO and provide intensive symptomatic treatment and monitoring.

5.4 Tardive Dyskinesia

Tardive dyskinesia, a syndrome of potentially irreversible, involuntary, dyskinetic movements may develop in patients treated with antipsychotic drugs, including SECUADO. The risk appears to be highest among the elderly, especially elderly women, but it is not possible to predict which patients are likely to develop the syndrome. Whether antipsychotic drug products differ in their potential to cause tardive dyskinesia is unknown.

The risk of developing tardive dyskinesia and the likelihood that it will become irreversible increases with the duration of treatment and the cumulative dose. The syndrome can develop after a relatively brief treatment period, even at low doses. It may also occur after discontinuation of treatment.

Tardive dyskinesia may remit, partially or completely, if antipsychotic treatment is discontinued. Antipsychotic treatment itself, however, may suppress (or partially suppress) the signs and symptoms of the syndrome, possibly masking the underlying process. The effect that symptomatic suppression has upon the long-term course of tardive dyskinesia is unknown.

Given these considerations, SECUADO should be prescribed in a manner that is most likely to reduce the risk of tardive dyskinesia. Chronic antipsychotic treatment should generally be reserved for patients: (1) who suffer from a chronic illness that is known to respond to antipsychotic drugs; and (2) for whom alternative, effective, but potentially less harmful treatments are not available or appropriate. In patients who do require chronic treatment, use the lowest dose and the shortest duration of treatment producing a satisfactory clinical response should be sought. Periodically reassess the need for continued treatment.

If signs and symptoms of tardive dyskinesia appear in a patient on SECUADO, drug discontinuation should be considered. However, some patients may require treatment with SECUADO despite the presence of the syndrome.

5.5 Metabolic Changes

Atypical antipsychotic drugs, including SECUADO, have caused metabolic changes, including hyperglycemia, diabetes mellitus, dyslipidemia, and body weight gain. Although all of the drugs in the class to date have been shown to produce some metabolic changes, each drug has its own specific risk profile.

Hyperglycemia and Diabetes Mellitus

Hyperglycemia, in some cases extreme and associated with ketoacidosis or hyperosmolar coma or death, has been reported in patients treated with atypical antipsychotics. There have been reports of hyperglycemia in patients treated with sublingual asenapine. Assess fasting plasma glucose before or soon after initiation of antipsychotic medication, and monitor periodically during long-term treatment.

Reports of hyperglycemia in patients treated with SECUADO were <1% in the placebo-controlled trial. Data from the placebo-controlled schizophrenia trial are presented in Table 1.

Table 1: Changes in Fasting Glucose in Adult Patients in the 6-Week, Placebo-Controlled, Fixed Dose Schizophrenia Trial
 | Placebo | SECUADO
 | Placebo | 3.8 mg/24 hours | 7.6 mg/24 hours
Mean Change from Baseline in Fasting Glucose at Endpoint
Change from Baseline (mg/dL) (N*) | 0.03 (174) | 3.28 (174) | 3.72 (172)
Proportion of Patients with Shifts from Baseline to Endpoint
Normal to High <100 to ≥ 126 mg/dL(n/N*) | 0% (0/198) | 3.1% (6/196) | 3.0% (6/199)
Borderline to High ≥100 and < 126 to ≥126 mg/dL (n/N*) | 2.0% (4/198) | 1.0% (2/196) | 1.0% (2/199)
N* = Number of patients who had assessments at both Baseline and Endpoint.

In the sublingual asenapine 52-week, double-blind, comparator-controlled trial that included primarily patients with schizophrenia, the mean increase from baseline of fasting glucose was 2.4 mg/dL.

Dyslipidemia

Atypical antipsychotics cause adverse alterations in lipids. Before or soon after initiation of antipsychotic medication, obtain a fasting lipid profile at baseline and monitor periodically during treatment.

Data from the placebo-controlled schizophrenia trial presented in Table 2.

Table 2: Changes in Lipids in Adult Patients in the 6-Week, Placebo-Controlled, Fixed Dose Schizophrenia Trial
 | Placebo | SECUADO
 | Placebo | 3.8 mg/24 hours | 7.6 mg/24 hours
Mean Change from Baseline
Total Cholesterol (mg/dL) (N*) | 0.7 (174) | 5.1 (174) | 4.5 (172)
LDL (mg/dL) (N*) | 1.6 (172) | 1.4 (170) | 4.2 (169)
HDL (mg/dL) (N*) | -0.8 (174) | 0.2 (174) | -0.7 (172)
Fasting triglycerides (mg/dL) (N*) | -2.6 (174) | 17.3 (174) | 6.7 (172)
Proportion of Patients with Shifts from Baseline to Endpoint(n/N*)
Total Cholesterol Normal to High <200 to ≥240 mg/dL (n/N*) | 1.0% (2/197) | 2.6% (5/196) | 1.0% (2/199)
LDL Normal to High <100 to ≥160 mg/dL (n/N*) | 0.5% (1/195) | 1.0% (2/194) | 0% (0/197)
HDL Normal to High ≥40 to <40 mg/dL (n/N*) | 8.1% (16/197) | 10.7% (21/196) | 12.1% (24/199)
Fasting Triglycerides Normal to High <150 to ≥200 mg/dL (n/N*) | 1.1% (2/185) | 7.0% (13/185) | 3.2% (6/186)
N* = Number of patients who had assessments at both Baseline and Endpoint.

In the placebo-controlled schizophrenia trial with SECUADO, the proportion of patients with total cholesterol elevations ≥240 mg/dL (at Endpoint) was 10.7% for patients treated with SECUADO 3.8 mg/24 hours and 13.6% for patients treated with SECUADO 7.6 mg/24 hours versus 10.2 % for placebo-treated patients. The proportion of patients with elevations in triglycerides ≥200 mg/dL (at Endpoint) was 17.8% for SECUADO 3.8 mg/24 hours and 12.4% for SECUADO 7.6 mg/24 hours treated patients versus 10.3% for placebo-treated patients.

Weight Gain

Weight gain has been observed with atypical antipsychotic use, including SECUADO. Monitor weight at baseline and frequently thereafter.

Data on mean changes in body weight and the proportion of subjects meeting a weight gain criterion of ≥7% of body weight from the placebo-controlled schizophrenia trial are presented in Table 3.

Table 3: Change in Body Weight in Adult Patients from Baseline in the 6-Week, Placebo-Controlled, Fixed Dose Schizophrenia Trial
 | Placebo | SECUADO
 | Placebo | 3.8 mg/24 hours | 7.6 mg/24 hours
Mean Change from Baseline (kg) (N*) | 0.62 (167) | 2.10 (168) | 2.02 (164)
Proportion of Patients with a ≥7% Increase in Body Weight
% with ≥7% increase in body weight (n/N*) | 3.9% (8/203) | 18.3% (37/202) | 14.3% (29/203)
N* = Number of subjects with data at Endpoint.

In the sublingual asenapine 52-week, double-blind, comparator-controlled adult trial that included primarily patients with schizophrenia, the mean weight gain from baseline was 0.9 kg. The proportion of patients with a ≥7% increase in body weight (at Endpoint) was 14.7%. Table 4 provides the mean weight change from baseline and the proportion of patients with a weight gain of ≥7% categorized by Body Mass Index (BMI) at baseline.

Table 4: Weight Change Results Categorized by BMI at Baseline: Comparator-Controlled 52-Week Study with Sublingual Asenapine in Adults with Schizophrenia
 | BMI <23 Sublingual Asenapine N=295 | BMI 23 - ≤27 Sublingual Asenapine N=290 | BMI >27 Sublingual Asenapine N=302
Mean Change from Baseline (kg) | 1.7 | 1 | 0
% with ≥7% increase in body weight | 22% | 13% | 9%

5.6 Hypersensitivity Reactions

Hypersensitivity reactions have been observed in patients treated with asenapine, including SECUADO. In several cases, these reactions occurred after the first dose. These hypersensitivity reactions included: anaphylaxis, angioedema, hypotension, tachycardia, swollen tongue, dyspnea, wheezing and rash.

5.7 Orthostatic Hypotension, Syncope, and Other Hemodynamic Effects

Atypical antipsychotics cause orthostatic hypotension and syncope. Generally, the risk is greatest during initial dose titration and when increasing the dose.

In the placebo-controlled trial, orthostatic hypotension was reported in 1.5% (3/204) of patients treated with SECUADO 3.8 mg/24 hours and 0% (0/204) of patients treated with SECUADO 7.6 mg/24 hours, compared to <1% (1/206) of patients treated with placebo.

There were no reports of syncope for both doses of SECUADO in the placebo-controlled trial.

During adult pre-marketing clinical trials with sublingual asenapine, including long-term trials without comparison to placebo, syncope was reported in 0.6% (11/1953) of patients treated with sublingual asenapine.

Orthostatic vital signs should be monitored in patients who are vulnerable to hypotension (elderly patients, patients with dehydration, hypovolemia, concomitant treatment with antihypertensive medications), patients with known cardiovascular disease (history of myocardial infarction or ischemic heart disease, heart failure, or conduction abnormalities), and patients with cerebrovascular disease. SECUADO should be used cautiously when treating patients who receive treatment with other drugs that can induce hypotension, bradycardia, respiratory or central nervous system depression [see Drug Interactions (7.1)]. Monitoring of orthostatic vital signs should be considered in all such patients, and a dose reduction should be considered if hypotension occurs.

5.8 Falls

SECUADO may cause somnolence, postural hypotension, motor and sensory instability, which may lead to falls and, consequently, fractures or other injuries. For patients with diseases, conditions, or medications that could exacerbate these effects, complete fall risk assessments when initiating antipsychotic treatment and recurrently for patients on long-term antipsychotic therapy.

5.9 Leukopenia, Neutropenia, and Agranulocytosis

In clinical trials and/or postmarketing experience, events of leukopenia and neutropenia have been reported temporally related to antipsychotic agents, including asenapine. Agranulocytosis (including fatal cases) has also been reported with other agents in the class.

Possible risk factors for leukopenia/neutropenia include pre-existing low white blood cell count (WBC) or absolute neutrophil count (ANC) and history of drug-induced leukopenia/neutropenia. In patients with pre-existing low WBC or ANC or history of drug-induced leukopenia or neutropenia, perform a complete blood count (CBC) frequently during the first few months of therapy. In such patients, consider discontinuation of SECUADO at the first sign of a clinically significant decline in WBC in the absence of other causative factors.

Monitor patients with clinically significant neutropenia for fever or other symptoms or signs of infection and treat promptly if such symptoms or signs occur. Discontinue SECUADO in patients with severe neutropenia (absolute neutrophil count <1000/mm^3) and follow their WBC until recovery.

5.10 QT Prolongation

The effects of sublingual asenapine on the QT/QTc interval were evaluated in a dedicated adult QT study. This trial involved sublingual asenapine doses of 5 mg, 10 mg, 15 mg, and 20 mg twice daily, and placebo, and was conducted in 151 clinically stable patients with schizophrenia, with electrocardiographic assessments throughout the dosing interval at baseline and steady state. At these doses, sublingual asenapine was associated with increases in QTc interval ranging from 2 to 5 msec compared to placebo. No patients treated with sublingual asenapine experienced QTc increases ≥60 msec from baseline measurements, nor did any patient experience a QTc of ≥500 msec.

Electrocardiogram (ECG) measurements were taken at various time points during the SECUADO clinical trial (3.8 mg/24 hours and 7.6 mg/24 hours doses). In the placebo-controlled trial, there were no reports of QT prolongations exceeding 500 msec for SECUADO and placebo.

There were no reports of Torsades de Pointes or any other adverse reactions associated with delayed ventricular repolarization with sublingual asenapine or with SECUADO.

The use of SECUADO should be avoided in combination with other drugs known to prolong QTc including Class 1A antiarrhythmics (e.g., quinidine, procainamide) or Class 3 antiarrhythmics (e.g., amiodarone, sotalol), antipsychotic medications (e.g., ziprasidone, chlorpromazine, thioridazine), and antibiotics (e.g., gatifloxacin, moxifloxacin). SECUADO should also be avoided in patients with a history of cardiac arrhythmias and in other circumstances that may increase the risk of the occurrence of torsade de pointes and/or sudden death in association with the use of drugs that prolong the QTc interval, including bradycardia; hypokalemia or hypomagnesemia; and presence of congenital prolongation of the QT interval.

5.11 Hyperprolactinemia

Like other drugs that antagonize dopamine D2 receptors, SECUADO can elevate prolactin levels, and the elevation can persist during chronic administration. Hyperprolactinemia may suppress hypothalamic GnRH, resulting in reduced pituitary gonadotropin secretion. This, in turn, may inhibit reproductive function by impairing gonadal steroidogenesis in both female and male patients. Galactorrhea, amenorrhea, gynecomastia, and impotence have been reported in patients receiving prolactin-elevating compounds. Long-standing hyperprolactinemia when associated with hypogonadism may lead to decreased bone density in both female and male subjects.

In the SECUADO placebo-controlled trial, galactorrhea, amenorrhea, gynecomastia, and impotence were not reported for patients treated with SECUADO or placebo [see Adverse Reactions (6.1)].

In sublingual asenapine adult pre-marketing clinical trials, the incidences of adverse events related to abnormal prolactin levels were 0.4% versus 0% for placebo.

Tissue culture experiments indicate that approximately one-third of human breast cancers are prolactin-dependent in vitro, a factor of potential importance if the prescription of these drugs is considered in a patient with previously-detected breast cancer. Published epidemiologic studies have shown inconsistent results when exploring the potential association between hyperprolactinemia and breast cancer.

5.12 Seizures

In the SECUADO placebo-controlled trial, there were no reports of seizures in adult patients treated with doses of 3.8 mg/24 hours and 7.6 mg/24 hours of SECUADO.

During adult pre-marketing clinical trials with sublingual asenapine, including long-term trials without comparison to placebo, seizures were reported in 0.3% (5/1953) of patients treated with sublingual asenapine.

As with other antipsychotic drugs, SECUADO should be used with caution in patients with a history of seizures or with conditions that potentially lower the seizure threshold. Conditions that lower the seizure threshold may be more prevalent in patients 65 years or older.

5.13 Potential for Cognitive and Motor Impairment

SECUADO, like other antipsychotics, has the potential to impair judgment, thinking or motor skills. Patients should be cautioned about operating hazardous machinery, including motor vehicles, until they are reasonably certain that SECUADO therapy does not affect them adversely.

Somnolence was reported in patients treated with SECUADO. In the short-term, fixed-dose, placebo-controlled schizophrenia adult trial, somnolence was reported in 4.4% (9/204) of patients on SECUADO 3.8 mg/24 hours and in 3.4% (7/204) of patients on SECUADO 7.6 mg/24 hours compared to 1.5% (3/206) of placebo patients. There were no reports of somnolence that led to discontinuation in the placebo-controlled trial.

During adult pre-marketing clinical trials with sublingual asenapine, including long-term trials without comparison to placebo, somnolence was reported in 18% (358/1953) of patients treated with sublingual asenapine.

5.14 Body Temperature Regulation

Atypical antipsychotics may disrupt the body’s ability to reduce core body temperature.

Strenuous exercise, exposure to extreme heat, dehydration, and anticholinergic medications may contribute to an elevation in core body temperature; use SECUADO with caution in patients who may experience these conditions.

5.15 Dysphagia

Esophageal dysmotility and aspiration have been associated with antipsychotic drug use. There were no reports of dysphagia with SECUADO; however, dysphagia has been reported with sublingual asenapine. SECUADO and other antipsychotic drugs should be used cautiously in patients at risk for aspiration.

5.16 External Heat

When heat is applied to SECUADO after application, both the rate and extent of absorption are increased. After application of a heating pad, asenapine exposure (partial AUC0-8) was about 3.9 times greater than without heating pad application [see Clinical Pharmacology (12.3)]. Advise patients to avoid exposing SECUADO to direct external heat sources such as hair dryers, heating pads, electric blankets, heated water beds, etc., while wearing SECUADO.

5.17 Application Site Reactions

Local skin reactions, such as irritation, were reported with SECUADO. During wear time or immediately after removal of SECUADO, the skin at the site of application may develop erythema, pruritus, papules, discomfort, pain, edema, or irritation. In the short-term, fixed-dose, placebo-controlled schizophrenia adult trial, application site reactions were reported in 15.2% (31/204) of patients on SECUADO 3.8 mg/24 hours and in 13.7% (28/204) of patients on SECUADO 7.6 mg/24 hours compared to 3.9% (8/206) of placebo patients. The most common application site reaction was erythema, which was reported in 9.3% (19/204) of patients on SECUADO 3.8 mg/24 hours and in 9.8% (20/204) of patients on SECUADO 7.6 mg/24 hours compared to 1.5% (3/206) of placebo patients. Another common application site reaction was pruritus, which was reported in 4.9% (10/204) of patients on SECUADO 3.8 mg/24 hours and in 3.9% (8/204) of patients on SECUADO 7.6 mg/24 hours compared to 1.9% (4/206) of placebo patients. One patient developed application site discoloration (hyperpigmentation) at multiple application sites that persisted for at least several weeks after discontinuing SECUADO treatment. Application site reactions occurred more frequently in Black or African American patients compared to Caucasians. Inform patients of these potential reactions and that increased skin irritation may occur with SECUADO if applied for a longer period than instructed or if the same application site is used repeatedly. Instruct patients to select a different application site each day to minimize skin reactions.

6 ADVERSE REACTIONS

The following adverse reactions are discussed in more detail in other sections of the labeling:

- Use in Elderly Patients with Dementia-Related Psychosis [see Warning and Precautions (5.1)]
- Cerebrovascular Adverse Reactions, Including Stroke, in Elderly Patients with Dementia-Related Psychosis [see Warnings and Precautions (5.2)]
- Neuroleptic Malignant Syndrome [see Warnings and Precautions (5.3)]
- Tardive Dyskinesia [see Warnings and Precautions (5.4)]
- Metabolic Changes [see Warnings and Precautions (5.5)]
- Hypersensitivity Reactions [see Contraindications(4), Warnings and Precautions (5.6) and Patient Counseling Information (17)]
- Orthostatic Hypotension, Syncope, and other Hemodynamic Effects [see Warnings and Precautions (5.7)]
- Falls [see Warnings and Precautions (5.8)]
- Leukopenia, Neutropenia, and Agranulocytosis [see Warnings and Precautions (5.9)]
- QT Interval Prolongation [see Warnings and Precautions (5.10)]
- Hyperprolactinemia [see Warnings and Precautions (5.11)]
- Seizures [see Warnings and Precautions (5.12)]
- Potential for Cognitive and Motor Impairment [see Warnings and Precautions (5.13)]
- Body Temperature Regulation [see Warnings and Precautions (5.14)]
- Dysphagia [see Warnings and Precautions (5.15)]
- External Heat [see Warnings and Precautions (5.16)]
- Application Site Reactions [see Warnings and Precautions (5.17)]

6.1 Clinical Trials Experience

Because clinical trials are conducted under widely varying conditions, adverse reaction rates observed in the clinical trials of a drug cannot be directly compared to rates in the clinical trials of another drug and may not reflect the rates observed in practice.

The safety of SECUADO was evaluated in a total of 315 adult patients diagnosed with schizophrenia who were exposed to SECUADO for up to 6 weeks in a placebo-controlled trial.

Adverse Reactions Leading to Discontinuation of Treatment

A total of 4.9% (10/204) patients treated with SECUADO 3.8 mg/24 hours, 7.8% (16/204) patients treated with SECUADO 7.6 mg/24 hours, and 6.8% (14/206) patients on placebo discontinued due to adverse reactions in the placebo-controlled trial. The adverse reaction that most commonly led to discontinuation among SECUADO-treated patients in this trial was akathisia, which led to discontinuation in no (0/204) patients treated with SECUADO 3.8 mg/24 hours, 1.5% (3/204) patients treated with SECUADO 7.6 mg/24 hours, and 0.5% (1/206) patients on placebo.

Commonly Observed Adverse Reactions

The most common adverse reactions (≥5% and at least twice the rate of placebo) reported in adult patients with schizophrenia treated with SECUADO in the placebo-controlled trial were extrapyramidal disorder, application site reaction and weight gain.

Adverse Reactions Occurring at an Incidence of 2% or More in SECUADO-Treated Patients.

Adverse reactions associated with the use of SECUADO (incidence of ≥2%, rounded to the nearest percent, and SECUADO incidence greater than placebo) that occurred during the placebo-controlled trial are shown in Table 5.

Table 5: Adverse Reactions in ≥2% of Patients in Any SECUADO Dose Group and Which Occurred at Greater Incidence Than in the Placebo Group in 6-Week Schizophrenia Trials
System Organ Class/ Preferred Term | Placebo N = 206 (%) | SECUADO
System Organ Class/ Preferred Term | Placebo N = 206 (%) | 3.8 mg/24 hours N = 204 (%) | 7.6 mg/24 hours N = 204 (%)
Gastrointestinal disorders
Constipation | 4 | 5 | 4
Dyspepsia | 1 | 1 | 3
Diarrhea | 1 | 3 | 1
General Disorders
Application Site Reactions* | 4 | 15 | 14
Investigations
Blood glucose increased* | 1 | 3 | 1
Weight Increased | 2 | 4 | 6
Hepatic enzyme increased* | 0 | 2 | 2
Infections and Infestations
Nasopharyngitis | 2 | 3 | 1
Upper respiratory tract infection | 2 | 3 | 1
Metabolism and nutrition disorders
Increased appetite | 0 | 3 | 1
Nervous System Disorders
Headache | 6 | 9 | 9
Extrapyramidal symptoms* | 2 | 8 | 13
Akathisia | 2 | 4 | 4
Somnolence* | 1 | 4 | 3
Dystonia | 0 | 1 | 3
Vascular Disorders
Hypertension* | 1 | 2 | 2
* The following terms were combined:
Application site reactions includes application site dermatitis, discoloration, discomfort, dryness, edema, erythema, exfoliation, induration, irritation, pain, papules, pruritus, and reaction.
Blood glucose increased includes blood glucose increased, blood insulin increased, glycosylated hemoglobin increased, hyperglycemia, Type 2 diabetes mellitus, diabetes mellitus, and hyperinsulinemia.
Hepatic enzyme increased includes hepatic enzyme increased, alanine aminotransferase increased, aspartate aminotransferase increased, and gamma-glutamyltransferase increased.
Extrapyramidal symptoms includes dyskinesia, dystonia, extrapyramidal disorder, parkinsonism. tardive dyskinesia, muscle spasm, and musculoskeletal stiffness.
Somnolence includes somnolence, sedation, lethargy, and hypersomnia.
Hypertension includes hypertension, blood pressure increased, diastolic hypertension, and hypertensive crisis.

Dose-Related Adverse Reactions: In the placebo-controlled schizophrenia trial, the incidence of an extrapyramidal disorder and weight increased appear to be dose-related (see Table 5).

Dystonia:

Symptoms of dystonia, prolonged abnormal contractions of muscle groups, may occur in susceptible individuals during the first few days of treatment. Dystonic symptoms include: spasm of the neck muscles, sometimes progressing to tightness of the throat, swallowing difficulty, difficulty breathing, and/or protrusion of the tongue. While these symptoms can occur at low doses, they occur more frequently and with greater severity with high potency and at higher doses of first generation antipsychotic drugs. An elevated risk of acute dystonia is observed in males and younger age groups [Clinical Pharmacology (12.3)].

Extrapyramidal Symptoms:

In the short-term, placebo-controlled schizophrenia adult trial, data were objectively collected on the Simpson Angus Rating Scale for extrapyramidal symptoms (EPS), the Barnes Akathisia Scale (for akathisia) and the Assessments of Involuntary Movement Scales (for dyskinesias). The mean change from baseline for the SECUADO 3.8 mg/24 hours or 7.6 mg/24 hours treated group was similar to placebo in each of the rating scale scores.

In the short-term, placebo-controlled schizophrenia adult trial, the incidence of reported extrapyramidal disorder events, excluding events related to akathisia, was 7.8% for patients treated with SECUADO 3.8 mg/24 hours, 12.8% for patients treated with SECUADO 7.6 mg/24 hours and 2.4% for placebo-treated patients; and the incidence of akathisia-related events was 3.9% for patients treated with SECUADO 3.8 mg/24 hours, 4.4% for patients treated with SECUADO 7.6 mg/24 hours and 2.4% for placebo-treated patients.

Laboratory Test Abnormalities:

Transaminases: Transient elevations in serum transaminases (primarily ALT) were more common in SECUADO-treated patients. The mean increase in ALT levels for SECUADO-treated patients was 6.0 units/L and 3.8 units/L for the SECUADO 3.8 mg/24 hours and 7.6 mg/24 hours treated groups, respectively, compared to a decrease of 1.1 units/L for placebo-treated patients. The proportion of patients with ALT elevations ≥3 times upper limit of normal (ULN) (at any time) was 1.6% and 3.1% for patients treated with SECUADO 3.8 mg/24 hours and 7.6 mg/24 hours, respectively, and 0% for placebo-treated patients.

In a 52-week, double-blind, comparator-controlled trial that included primarily adult patients with schizophrenia, the mean increase from baseline of ALT was 1.7 units/L for sublingual asenapine.

Prolactin: The proportion of patients with prolactin elevations ≥4 times ULN (at Endpoint) were 0.0% and 1.3% for patients treated with SECUADO 3.8 mg/24 hours and 7.6 mg/24 hours, respectively, as compared to 2.4% for placebo-treated patients in the short-term placebo-controlled trial.

In a long-term (52-week), double-blind, comparator-controlled adult trial that included primarily patients with schizophrenia, the mean decrease in prolactin from baseline for sublingual asenapine-treated patients was 26.9 ng/mL.

Creatine Kinase (CK): The proportion of adult patients with CK elevations ≥3 times ULN at any time were 1.6% and 2.1% for patients treated with SECUADO 3.8 mg/24 hours and 7.6 mg/24 hours, respectively, as compared to 1.5% for placebo-treated patients in the short-term, placebo-controlled trial. The clinical relevance of this finding is unknown.

Other Adverse Reactions Observed During the Premarketing Evaluation of SECUADO

Other adverse reactions (<2% frequency) within the 6-week placebo-controlled trial in patients with schizophrenia are listed below. The reactions listed are those that could be of clinical importance, as well as reactions that are plausibly drug-related on pharmacologic or other grounds. Reactions that appear elsewhere in the SECUADO label are not included.

Gastrointestinal disorders: vomiting, dry mouth

General disorders and administration site conditions: asthenia

Musculoskeletal and connective tissue disorders: myalgia

Other Adverse Reactions Reported in Clinical Trials with Sublingual Asenapine

Following is a list of MedDRA terms that reflect adverse reactions reported by patients treated with sublingual asenapine at multiple doses of ≥5 mg twice daily during any phase of a trial within the database of adult patients. The reactions listed are those that could be of clinical importance, as well as reactions that are plausibly drug-related on pharmacologic or other grounds. Reactions already listed for adult patients in other parts of Adverse Reactions (6), or those considered in Contraindications (4), Warnings and Precautions (5) or Overdosage (10) are not included. Reactions are further categorized by MedDRA system organ class and listed in order of decreasing frequency according to the following definitions: those occurring in at least 1/100 patients (frequent) (only those not already listed in the tabulated results from placebo-controlled trials appear in this listing); those occurring in 1/100 to 1/1000 patients (infrequent); and those occurring in fewer than 1/1000 patients (rare).

Blood and lymphatic disorders: infrequent: anemia; rare: thrombocytopenia

Cardiac disorders: infrequent: temporary bundle branch block

Eye disorders: infrequent: accommodation disorder

Gastrointestinal disorders: infrequent: swollen tongue

General disorders: rare: idiosyncratic drug reaction

Investigations: infrequent: hyponatremia

Nervous system disorders: infrequent: dysarthria

6.2 Postmarketing Experience

The following adverse reactions have been identified during post-approval use of sublingual asenapine and are possible with SECUADO treatment. Because these reactions are reported voluntarily from a population of uncertain size, it is not always possible to establish a causal relationship to drug exposure.

- Choking has been reported by patients, some of whom may have also experienced oropharyngeal muscular dysfunction.

7 DRUG INTERACTIONS

7.1 Drugs Having Clinically Important Drug Interactions with SECUADO

Table 6: Clinically Important Drug Interactions with SECUADO
Antihypertensive Drugs
Clinical Implication | Because of its α1-adrenergic antagonism with potential for inducing hypotension, SECUADO may enhance the effects of certain antihypertensive agents [see Warnings and Precautions (5.7)].
Prevention or Management: | Monitor blood pressure and adjust dosage of antihypertensive drug accordingly.
Examples: | Diuretics, ACE Inhibitors, Angiotensin Receptor Blockers, and Beta-Blockers, Alpha-blockers
Strong CYP1A2 Inhibitors
Clinical Implication | Asenapine is metabolized by CYP1A2. Concomitant use of SECUADO with a CYP1A2 inhibitor increases AUC and Cmax of asenapine [see Clinical Pharmacology (12.3)].
Prevention or Management: | Dosage reduction for SECUADO based on clinical response may be necessary.
Examples: | Fluvoxamine, ciprofloxacin, enoxacin
CYP2D6 substrates and inhibitors
Clinical Implication | Asenapine may enhance the inhibitory effects of paroxetine on its own metabolism by CYP2D6. Concomitant use of SECUADO with paroxetine increases paroxetine AUC and Cmax [see Clinical Pharmacology (12.3)].
Prevention or Management: | Reduce paroxetine dose by half when paroxetine is used in combination with SECUADO.
Examples: | Paroxetine

8 USE IN SPECIFIC POPULATIONS

8.1 Pregnancy

Pregnancy Exposure Registry

There is a pregnancy exposure registry that monitors pregnancy outcomes in women exposed to atypical antipsychotics, including SECUADO, during pregnancy. For more information contact the National Pregnancy Registry for Atypical Antipsychotics at 1-866-961-2388 or visit http://womensmentalhealth.org/clinical-and-research-programs/pregnancyregistry/.

Risk Summary

Neonates exposed to antipsychotic drugs during the third trimester of pregnancy are at risk for extrapyramidal and/or withdrawal symptoms. Studies have not been conducted with SECUADO in pregnant women. There are no available human data informing the drug-associated risk. The background risk of major birth defects and miscarriage for the indicated populations are unknown. However, the background risk in the U.S. general population of major birth defects is 2-4% and of miscarriage is 15-20% of clinically recognized pregnancies. No teratogenicity was observed in animal reproduction studies with intravenous administration of asenapine to rats and rabbits during organogenesis at doses 0.7 and 0.4 times, respectively, the maximum recommended human dose (MRHD) of 10 mg of sublingual asenapine twice daily and 1.1 and 0.66 times, respectively, the MRHD of 12.8 mg of transdermal asenapine daily. In a pre-and post-natal study in rats, intravenous administration of asenapine at doses up to 0.7 times the MRHD of 10 mg of sublingual asenapine twice daily produced increases in post-implantation loss and early pup deaths, and decreases in subsequent pup survival and weight gain [see Data]. These doses are up to 1.1 times the MRHD of 12.8 mg transdermal asenapine daily. Advise pregnant women of the potential risk to a fetus.

Clinical Considerations

Fetal/Neonatal Adverse Reactions

Extrapyramidal and/or withdrawal symptoms, including agitation, hypertonia, hypotonia, tremor, somnolence, respiratory distress and feeding disorder have been reported in neonates who were exposed to antipsychotic drugs during the third trimester of pregnancy. These symptoms have varied in severity. Some neonates recovered within hours or days without specific treatment; others required prolonged hospitalization. Monitor neonates for extrapyramidal and/or withdrawal symptoms and manage symptoms appropriately.

Data

Animal Data

In animal studies, asenapine increased post-implantation loss and decreased pup weight and survival at doses similar to or less than recommended clinical doses. In these studies, there was no increase in the incidence of structural abnormalities caused by asenapine.

Asenapine was not teratogenic in reproduction studies in rats and rabbits at intravenous doses up to 1.5 mg/kg in rats and 0.44 mg/kg in rabbits administered during organogenesis. These doses are 0.7 and 0.4 times, respectively, MRHD of 10 mg of sublingual asenapine twice daily and 1.1 and 0.66 times, respectively, the MRHD of 12.8 mg transdermal asenapine daily. Plasma levels of asenapine were measured in the rabbit study, and the area under the curve (AUC) at the highest dose tested was 2 times that in humans receiving the MRHD of 10 mg of sublingual asenapine twice daily.

In a study in which rats were treated from day 6 of gestation through day 21 postpartum with intravenous doses of asenapine of 0.3, 0.9, and 1.5 mg/kg/day (0.15, 0.44, and 0.7 times the MRHD of 10 mg of sublingual asenapine twice daily and 0.22, 0.68 and 1.13 times the MRHD of 12.8 mg transdermal asenapine daily), increases in post-implantation loss and early pup deaths were seen at all doses, and decreases in subsequent pup survival and weight gain were seen at the two higher doses. A cross-fostering study indicated that the decreases in pup survival were largely due to prenatal drug effects. Increases in post-implantation loss and decreases in pup weight and survival were also seen when pregnant rats were dosed orally with asenapine.

8.2 Lactation

Risk Summary

Lactation studies have not been conducted to assess the presence of asenapine in human milk, the effects of asenapine on the breastfed infant, or the effects of asenapine on milk production. Asenapine is excreted in rat milk. The development and health benefits of breastfeeding should be considered along with the mother's clinical need for SECUADO and any potential adverse effects on the breastfed infant from SECUADO or from the underlying maternal condition.

8.4 Pediatric Use

Safety and effectiveness of SECUADO in pediatric patients have not been established.

Efficacy of sublingual asenapine was not demonstrated in an 8-week, placebo-controlled, double-blind trial, in 306 adolescent patients aged 12 to 17 years with schizophrenia at doses of 2.5 and 5 mg twice daily. The most common adverse reactions (proportion of patients equal or greater than 5% and at least twice placebo) reported were somnolence, akathisia, dizziness, and oral hypoesthesia or paresthesia. The proportion of patients with an equal or greater than 7% increase in body weight at endpoint compared to baseline for placebo, sublingual asenapine 2.5 mg twice daily, and sublingual asenapine 5 mg twice daily was 3%, 10%, and 10%, respectively. No new major safety findings were reported from a 26-week, open-label, uncontrolled safety trial in pediatric patients with schizophrenia treated with sublingual asenapine.

Juvenile Animal Data

Subcutaneous administration of asenapine to juvenile rats for 56 days from day 14 of age to day 69 of age at 0.4, 1.2, and 3.2 mg/kg/day (0.2, 0.6 and 1.5 times the maximum recommended human dose of 10 mg twice daily given sublingually on a mg/m^2 basis) resulted in significant reduction in body weight gain in animals of both sexes at all dose levels from the start of dosing until weaning. Body weight gain remained reduced in males to the end of treatment, however, recovery was observed once treatment ended. Neurobehavioral assessment indicated increased motor activity in animals at all dose levels following the completion of treatment, with the evidence of recovery in males. There was no recovery after the end of treatment in female activity pattern as late as day 30 following the completion of treatment (last retesting). Therefore, a No Observed Adverse Effect Level (NOAEL) for the juvenile animal toxicity of asenapine could not be determined. There were no treatment-related effects on the startle response, learning/memory, organ weights, microscopic evaluations of the brain and, reproductive performance (except for minimally reduced conception rate and fertility index in males and females administered 1.2 and 3.2 mg/kg/day).

8.5 Geriatric Use

The SECUADO placebo-controlled trial for the treatment of schizophrenia did not include sufficient numbers of patients aged 65 and over to determine whether or not they respond differently than younger patients. Of the approximately 614 patients in placebo-controlled study of SECUADO, 1.6% (10) were 65 years of age or over.

Multiple factors that might increase the pharmacodynamic response to SECUADO, causing poorer tolerance or orthostasis, could be present in elderly patients, and these patients should be monitored carefully. Based on a pharmacokinetic study in elderly patients with sublingual asenapine, dosage adjustments are not recommended based on age alone [see Clinical Pharmacology (12.3)].

Elderly patients with dementia-related psychosis treated with SECUADO are at an increased risk of death compared to placebo. SECUADO is not approved for the treatment of patients with dementia-related psychosis [see Warning and Precautions (5.1, 5.2)].

8.6 Renal Impairment

No dosage adjustment for SECUADO is required on the basis of a patient’s renal function (mild to severe renal impairment, glomerular filtration rate between 15 and 90 mL/minute). The exposure of asenapine was similar among subjects with varying degrees of renal impairment and subjects with normal renal function [see Clinical Pharmacology (12.3)]. The effect of renal function on the excretion of other metabolites and the effect of dialysis on the pharmacokinetics of asenapine has not been studied.

8.7 Hepatic Impairment

SECUADO is contraindicated in patients with severe hepatic impairment (Child-Pugh C) because asenapine exposure is 7-fold higher in subjects with severe hepatic impairment than the exposure observed in subjects with normal hepatic function.

No dosage adjustment for SECUADO is required in patients with mild to moderate hepatic impairment (Child-Pugh A and B) because asenapine exposure is similar to that in subjects with normal hepatic function [see Contraindications (4) and Clinical Pharmacology (12.3)].

9 DRUG ABUSE AND DEPENDENCE

9.1 Controlled Substance

SECUADO is not a controlled substance.

9.2 Abuse

SECUADO has not been systematically studied in animals or humans for its abuse potential or its ability to induce tolerance or physical dependence. Thus, it is not possible to predict the extent to which a CNS-active drug will be misused, diverted and/or abused once it is marketed. Patients should be evaluated carefully for a history of drug abuse, and such patients should be observed carefully for signs that they are misusing or abusing SECUADO (e.g., drug-seeking behavior, increases in dose).

10 OVERDOSAGE

Human Experience: In the placebo-controlled trial in adults for SECUADO, there were no reports of accidental or intentional acute overdosage of SECUADO.

In adult clinical studies involving more than 3350 patients and/or healthy subjects for sublingual asenapine, accidental or intentional acute overdosage of sublingual asenapine was identified in 3 patients. Among these few reported cases of overdose, the highest estimated ingestion of sublingual asenapine was 400 mg. Reported adverse reactions at the highest dosage included agitation and confusion.

Management of Overdosage: There is no specific antidote to SECUADO. The possibility of multiple drug involvement should be considered. An electrocardiogram should be obtained and management of overdose should concentrate on supportive therapy, maintaining an adequate airway, oxygenation and ventilation, and management of symptoms. Consult a Certified Poison Control Center at 1 800-222-1222 for up to date information on the management of overdosage.

Hypotension and circulatory collapse should be treated with appropriate measures, such as intravenous fluids and/or sympathomimetic agents (epinephrine and dopamine should not be used, since beta stimulation may worsen hypotension in the setting of SECUADO-induced alpha blockade). In case of severe extrapyramidal symptoms, anticholinergic medication should be administered. Close medical supervision and monitoring should continue until the patient recovers.

11 DESCRIPTION

SECUADO transdermal system contains asenapine, an atypical antipsychotic.

Asenapine belongs to the class dibenzo-oxepino pyrroles. The chemical name is trans-5-chloro-2-methyl-2,3,3a,12b-tetrahydro-1H-dibenz[2,3:6,7] oxepino [4,5-c] pyrrole. Its molecular formula is C17H16Cl NO and its molecular weight is 285.8 g/mol. The chemical structure is:

SECUADO is for transdermal administration and is provided in three strengths: 3.8 mg, 5.7 mg or 7.6 mg asenapine every 24 hours (Table 7). The composition of the transdermal systems per unit area is identical. Inactive ingredients include alicyclic saturated hydrocarbon resin, butylated hydroxytoluene, isopropyl palmitate, maleate salts (monosodium maleate and disodium maleate), mineral oil, polyester film backing, polyisobutylene, silicone-treated polyester release liner, sodium acetate anhydrous, and styrene-isoprene-styrene block copolymer.

Table 7: SECUADO (asenapine) transdermal system
Dosage Strength (Asenapine) | Total Asenapine Content per Transdermal System | Transdermal System Size
3.8 mg/24 hours | 6.4 mg | 20 cm^2
5.7 mg/24 hours | 9.6 mg | 30 cm^2
7.6 mg/24 hours | 12.8 mg | 40 cm^2

12 CLINICAL PHARMACOLOGY

12.1 Mechanism of Action

The mechanism of action of asenapine in schizophrenia is unclear. However, it’s efficacy in schizophrenia could be mediated through a combination of antagonist activity at D2 and 5-HT2A receptors.

12.2 Pharmacodynamics

Asenapine exhibits high affinity for serotonin 5-HT1A, 5-HT1B, 5-HT2A, 5-HT2B, 5-HT2C, 5-HT5A, 5-HT6 and 5-HT7 receptors (Ki values of 2.5, 2.7, 0.07, 0.18, 0.03, 1.6, 0.25, and 0.11nM, respectively), dopamine D2A, D2B, D3, D4, and D1 receptors (Ki values of 1.3, 1.4, 0.42, 1.1, and 1.4 nM, respectively), adrenergic α1A, α2A, α2B, and α2C receptors (Ki values of 1.2, 1.2, 0.33 and 1.2 nM, respectively), and histamine H1 receptors (Ki value 1.0 nM), and moderate affinity for H2 receptors (Ki value of 6.2 nM). In in vitro assays asenapine acts as an antagonist at these receptors. Asenapine has no appreciable affinity for muscarinic cholinergic receptors (e.g., Ki value of 8128 nM for M1).

12.3 Pharmacokinetics

SECUADO has a different pharmacokinetic profile compared to sublingual asenapine. Maximum asenapine concentrations are typically reached between 12 and 24 hours, with sustained concentrations during wear time (24 hours). Following SECUADO removal, the apparent elimination half-life is approximately 30 hours.

Absorption

On average, approximately 60% of the asenapine is released from the transdermal system over 24 hours. Inter-individual variability for SECUADO as coefficient of variation (%CV) for the steady-state asenapine Cmax,ss, Cmin,ss, and AUC0-tau,ss was generally about 20% to 30%.

Asenapine PK at steady-state is dose-proportional in the dose range of 3.8 mg/24 hours to 7.6 mg/24 hours following application of SECUADO. Steady-state plasma concentrations are achieved in about 72 hours after the first application of SECUADO. Peak to trough ratio is 1.5.

Based on relative bioavailability and established dose proportionality, AUC for 3.8 mg/24 hours and 7.6 mg/24 hours was considered to be similar to that for sublingual asenapine 5 mg twice daily and 10 mg twice daily, respectively.

There is no effect on asenapine PK with regards to the application site (upper arm, upper back, abdomen, and hip area).

Application of a heating pad on SECUADO for 8 hours led to a faster absorption rate (median tmax about 8 hours) as compared with SECUADO without a heating pad (median tmax about 16 hours). Mean asenapine exposure, calculated as partial AUC0-8, following SECUADO application, was about 3.9 times greater than that without a heating pad, indicating the apparent heat effect in absorption during the time period of heating pad application.

Distribution

Asenapine is rapidly distributed and has a large volume of distribution (approximately 20-25 L/kg), indicating extensive extravascular distribution. Asenapine is highly bound (95%) to plasma proteins, including albumin and α1-acid glycoprotein.

Elimination

Asenapine is a high clearance drug with a clearance after intravenous administration of 52 L/h. In this circumstance, hepatic clearance is influenced primarily by changes in liver blood flow rather than by changes in the intrinsic clearance, i.e., the metabolizing enzymatic activity

Metabolism

Direct glucuronidation by UGT1A4 and oxidative metabolism by cytochrome P450 isoenzymes (predominantly CYP1A2) are the primary metabolic pathways for asenapine.

Excretion

After administration of a single dose of [^14C]-labeled asenapine, about 90% of the dose was recovered; approximately 50% was recovered in urine, and 40% recovered in feces. About 50% of the circulating species in plasma have been identified. The predominant species was asenapine N -glucuronide; others included N-desmethylasenapine, N-desmethylasenapine N-carbamoyl glucuronide, and unchanged asenapine in smaller amounts. Pharmacological activity is primarily due to the parent drug.

Special Populations

Exposures of asenapine in special populations for sublingual asenapine are summarized in Figure 1.

Based on population pharmacokinetic analysis for sublingual asenapine, no effects of sex, race, ethnicity (Japanese versus Caucasian), BMI, and smoking status on asenapine exposure were observed. Exposure in elderly patients is 30-40% higher as compared to adults.

Figure 1: Effect of Intrinsic Factors on Sublingual Asenapine Pharmacokinetics

Drug Interaction Studies

Effects of other drugs on the exposure of asenapine are summarized in Figure 2. Marginal increase of asenapine exposure was observed when sublingual asenapine is used with fluvoxamine at 25 mg administered twice daily. However, the tested fluvoxamine dose was suboptimal. Full therapeutic dose of fluvoxamine is expected to cause a greater increase in asenapine exposure.

Figure 2: Effect of Other Drugs on Asenapine Pharmacokinetics

The effects of asenapine on the pharmacokinetics of other co-administered drugs are summarized in Figure 3.

Figure 3: Effect of Asenapine on Other Drug Pharmacokinetics

In vitro studies indicate that asenapine is a substrate for UGT1A4, CYP1A2 and to a lesser extent CYP3A4 and CYP2D6. Asenapine is a weak inhibitor of CYP2D6. Asenapine does not cause induction of CYP1A2 or CYP3A4 activities in cultured human hepatocytes. Coadministration of asenapine with known inhibitors, inducers or substrates of these metabolic pathways has been studied in a number of drug-drug interaction studies [see Drug Interactions (7.1)].

13 NONCLINICAL TOXICOLOGY

13.1 Carcinogenesis, Mutagenesis, Impairment of Fertility

Carcinogenesis: In a lifetime carcinogenicity study in CD-1 mice asenapine was administered subcutaneously at doses up to those resulting in plasma levels (AUC) estimated to be 5 times those in humans receiving the MRHD of 10.0 mg twice daily. The incidence of malignant lymphomas was increased in female mice, with a no-effect dose resulting in plasma levels estimated to be 1.5 times those in humans receiving the MRHD. The mouse strain used has a high and variable incidence of malignant lymphomas, and the significance of these results to humans is unknown. There were no increases in other tumor types in female mice. In male mice, there were no increases in any tumor type.

In a lifetime carcinogenicity study in Sprague-Dawley rats, asenapine did not cause any increases in tumors when administered subcutaneously at doses up to those resulting in plasma levels (AUC) estimated to be 5 times those in humans receiving the MRHD.

In a 39-week study in minipigs, the asenapine transdermal system was administered at doses of 0.43 to 3.84 mg/kg asenapine, once every 24 hours. No significant dermal findings occurred at doses up to 17 times the MRHD of 12.8 mg transdermal asenapine daily for schizophrenia.

Mutagenesis: No evidence for genotoxic potential of asenapine was found in the in vitro bacterial reverse mutation assay, the in vitro forward gene mutation assay in mouse lymphoma cells, the in vitro chromosomal aberration assays in human lymphocytes, the in vitro sister chromatid exchange assay in rabbit lymphocytes, or the in vivo micronucleus assay in rats.

Impairment of Fertility: Asenapine did not impair fertility in rats when tested at doses up to 11 mg/kg twice daily given orally. This dose is 10 times MRHD of 10 mg twice daily asenapine given sublingually on a mg/m^2 basis and 16.6 times the MRHD of 12.8 mg daily asenapine given transdermally on a mg/m^2 basis.

13.2 Animal Toxicology and/or Pharmacology

Transdermal administration of asenapine to rats, dogs and minipigs did not demonstrate any significant dermal findings when applied daily for 24 hours. Rats were treated for 26-weeks with percutaneous doses of asenapine (as free base) up to 1.42 mg/kg (1.3 times the MRHD of 12.8 mg transdermal asenapine as free base daily on a mg/kg basis), dogs were treated for 13-weeks with percutaneous doses of asenapine (as free base) up to 5.6 mg/kg (14.2 times the MRHD of 12.8 mg transdermal asenapine daily on mg/m^2 basis) and minipigs were treated for 39-weeks with percutaneous doses of asenapine (as free base) up to 3.84 mg/kg (17 times the MRHD of 12.8 mg transdermal asenapine [as free base] daily on mg/m^2 basis).

14 CLINICAL STUDIES

The efficacy of SECUADO in the treatment of adult patients with schizophrenia was established, in part, on the basis of efficacy data from trials with the sublingual formulation of asenapine. In addition, the efficacy of SECUADO was evaluated in a 6-week, fixed-dose, randomized, double-blind, and placebo-controlled trial (Study 1; NCT 02876900) of adult patients who met DSM-IV criteria for schizophrenia.

In Study 1, the Positive and Negative Syndrome Scale (PANSS) and Clinical Global Impressions-Severity (CGI-S) rating scales were used as the primary and key secondary efficacy measures, respectively, for assessing psychiatric signs and symptoms in each trial:

- PANSS is a 30 item scale that measures positive symptoms of schizophrenia (7 items), negative symptoms of schizophrenia (7 items), and general psychopathology (16 items), each rated on a scale of 1 (absent) to 7 (extreme); total PANSS scores range from 30 to 210.
- CGI-S is a validated clinician-rated scale that measures the patient’s current illness state and overall clinical state on a 1 (normal, not at all ill) to 7-point (extremely ill) scale, based on the rater’s total clinical experience with this population.

The primary endpoint was change from baseline in PANSS total score to Week 6. The change from baseline for SECUADO was compared to that for placebo. The results of the trial are shown in Table 8. The time course of efficacy is shown in Figure 4.

In the 6-week trial (n=607) comparing two fixed doses of SECUADO (3.8 mg/24 hours and 7.6 mg/24 hours) to placebo, both doses were statistically superior to placebo for both PANSS total score and CGI-S.

An examination of population subgroups did not reveal any clear evidence of differential responsiveness on the basis of age, sex or race.

Table 8: Primary Efficacy Results for Change from Baseline in PANSS Total Score Week 6 (Study 1)
Treatment Group | Primary Efficacy Measure: PANSS Total Score
Treatment Group | Mean Baseline Score (SD) | LS Mean Change from Baseline (SE) to Week 6 | Placebo-subtracted Differencea (95% CI)
SECUADO 3.8 mg/24 hours* | 97.0 (9.78) | -22.1 (1.2) | -6.6 (-9.81, -3.40)
SECUADO 7.6 mg/24 hours* | 95.6 (8.68) | -20.4 (1.2) | -4.8 (-8.06, -1.64)
Placebo | 97.4 (10.07) | -15.5 (1.2) | --
SD: standard deviation; SE: standard error; LS Mean: least-squares mean; CI: confidence interval.
a Difference (drug minus placebo) in least-squares mean change from baseline. A negative value for the placebo subtracted difference represents improvement.
*: Statistically significant after multiplicity adjustments.

Figure 4: Change from Baseline in PANSS Total Score Over Time (Weeks) in Patients with Schizophrenia (Study 1)

Maintenance of Efficacy with Sublingual Asenapine

Maintenance of efficacy has been demonstrated in a placebo-controlled, double-blind, multicenter, flexible dose with sublingual asenapine (5 mg or 10 mg twice daily based on tolerability) clinical trial with a randomized withdrawal design. All patients were initially administered 5 mg twice daily for 1 week and then titrated up to 10 mg twice daily. A total of 700 patients entered open label treatment with sublingual asenapine for a period of 26 weeks. Of these, a total of 386 patients who met pre-specified criteria for continued stability (mean length of stabilization was 22 weeks) were randomized to a double-blind, placebo-controlled, randomized withdrawal phase. Sublingual asenapine was statistically superior to placebo in time to relapse or impending relapse defined as increase in PANSS ≥20% from baseline and a Clinical Global Impression–Severity of Illness (CGI-S) score ≥4 (at least 2 days within 1 week) or PANSS score ≥5 on "hostility" or "uncooperativeness" items and CGI-S score ≥4 (≥2 days within a week), or PANSS score ≥5 on any two of the following items: "unusual thought content," "conceptual disorganization," or "hallucinatory behavior" items, and CGI-S score ≥4 (≥2 days within 1 week) or investigator judgment of worsening symptoms or increased risk of violence to self (including suicide) or other persons.The Kaplan-Meier curves of the time to relapse or impending relapse during the randomized, double-blind, placebo-controlled withdrawal phase of this trial for asenapine and placebo are shown in Figure 5.

Figure 5: Kaplan-Meier Estimation of Percent Relapse for Sublingual Asenapine and Placebo

Adhesion

Based on a clinical study in 40 subjects, each wearing one SECUADO 3.8 mg/24 hours, 40 transdermal systems (100%) exhibited 75% or greater surface area adhesion at all timepoints evaluated (every 4 hours) throughout the 24-hour wear period. Based on a clinical study in 39 subjects, each wearing one SECUADO 7.6 mg/24 hours, 36 transdermal systems (92%) exhibited 75% or greater surface area adhesion at all timepoints evaluated (every 4 hours) throughout the 24-hour wear period. One SECUADO 7.6 mg/24 hours transdermal system worn on the hip fully detached.

16 HOW SUPPLIED/STORAGE AND HANDLING

16.1 How Supplied

SECUADO (asenapine) transdermal system is a translucent rounded square product with a printed backing on one side and a release liner on the other supplied as:

- 3.8 mg/24 hours transdermal system (system size: 20 cm^2)
  Carton of 30 transdermal systems, each transdermal system is packaged in an individual pouch
  NDC 68968-0172-3
- 5.7 mg/24 hours transdermal system (system size: 30 cm^2)
  Carton of 30 systems, each system is packaged into an individual pouch
  NDC 68968-0173-3
- 7.6 mg/24 hours transdermal system (system size: 40 cm^2)
  Carton of 30 transdermal systems, each transdermal system is packaged in an individual pouch
  NDC 68968-0174-3

16.2 Storage

Store at room temperature 20°C to 25°C (68°F to 77°F) with excursions permitted between 15°C and 30°C (between 59°F and 86°F) [see USP Controlled Room Temperature] .

17 PATIENT COUNSELING INFORMATION

Advise the patient to read the FDA-approved patient labeling (Instructions for Use).

Hypersensitivity Reactions

Counsel patients on the signs and symptoms of a serious allergic reaction (e.g., difficulty breathing, itching, swelling of the face, tongue or throat, feeling lightheaded etc.) and to seek immediate emergency assistance if they develop any of these signs and symptoms [see Contraindications (4), Warnings and Precautions (5.6)].

Neuroleptic Malignant Syndrome

Counsel patients about a potentially fatal adverse reaction referred to as NMS that has been reported in association with administration of antipsychotic drugs. Advise patients to contact a healthcare provider or report to the emergency room if they experience signs or symptoms of NMS including hyperpyrexia, muscle rigidity, altered mental status, and evidence of autonomic instability (irregular pulse or blood pressure, tachycardia, diaphoresis, and cardiac dysrhythmia) [see Warnings and Precautions (5.3)].

Tardive Dyskinesia

Counsel patients on the signs and symptoms of tardive dyskinesia and to contact their health care provider if these abnormal movements occur [see Warnings and Precautions (5.4)].

Metabolic Changes (Hyperglycemia and Diabetes Mellitus, Dyslipidemia, and Weight Gain)

Educate patients about the risk of metabolic changes, how to recognize symptoms of hyperglycemia (high blood sugar) and diabetes mellitus, and the need for specific monitoring, including blood glucose, lipids, and weight [see Warnings and Precautions (5.5)].

Orthostatic Hypotension

Counsel patients about the risk of orthostatic hypotension (symptoms include feeling dizzy or lightheaded upon standing) especially early in treatment, and at times of re-initiating treatment or increases in dose [see Warnings and Precautions (5.7)].

Leukopenia/Neutropenia

Advise patients with a pre-existing low WBC or a history of drug induced leukopenia/neutropenia they should have their CBC monitored while taking SECUADO [see Warnings and Precautions (5.9)].

Hyperprolactinemia

Counsel patients on the signs and symptoms of hyperprolactinemia and to contact their health care provider if these abnormalities occur [see Warnings and Precautions (5.11)].

Interference with Cognitive and Motor Performance

Caution patients about performing activities requiring mental alertness, such as operating hazardous machinery or operating a motor vehicle, until they are reasonably certain that SECUADO therapy does not affect them adversely [see Warnings and Precautions (5.13)].

Heat Exposure and Dehydration

Counsel patients regarding appropriate care in avoiding overheating and dehydration [see Warnings and Precautions (5.14)].

External Heat

Inform patients to avoid exposing SECUADO to external heat sources, such as hair dryers, heating pads, electric blankets, heated water beds, etc., [see Warnings and Precautions (5.16)].

Application Site Reactions

Inform patients that application site reactions, including erythema, pruritus, papules, discomfort, pain, edema or irritation, have been reported with use of SECUADO. Inform patients that increased skin irritation may occur if applied for a longer period than instructed or if the same application site is used repeatedly. Instruct patients to select a different application site each day to minimize skin reactions. Patients should monitor for these reactions while wearing or immediately after removal of SECUADO [see Warnings and Precautions (5.17)].

Concomitant Medications

Advise patients to inform their health care provider if they are taking, or plan to take, any prescription or over-the-counter medications since there is a potential for interactions [see Drug Interactions (7.1)].

Pregnancy

Advise patients that SECUADO may cause fetal harm as well as extrapyramidal and/or withdrawal symptoms in a neonate. Advise patients to notify their healthcare provider with a known or suspected pregnancy [see Use in Specific Populations (8.1)].

Pregnancy Registry

Advise patients that there is a pregnancy exposure registry that monitors pregnancy outcomes in women exposed to SECUADO during pregnancy [see Use in Specific Populations (8.1)].

Manufactured by: Hisamitsu Pharmaceutical Co. Inc., 408, Tashirodaikan-machi, Tosu, Saga, Japan

Distributed by: Noven Therapeutics, LLC, Miami, Florida USA.

For more information, call 1-800-455-8070 or visit www.secuado.com

SECUADO is a registered trademark of Hisamitsu Pharmaceutical Co., Inc.

©2019-2025 Hisamitsu Pharmaceutical Co., Inc. All rights reserved.

5O134A-0

Instructions for Use

SECUADO® (seh kue a’ doe)

(asenapine) transdermal system

Read this Instructions for Use before you start using the SECUADO transdermal system (patch) and each time you get a refill. There may be new information. This information does not take the place of talking to your healthcare provider about your medical condition or treatment.

Important Information:

- The SECUADO transdermal system (patch) is for use on the skin only (transdermal).
- Do not cut the pouch open until you are ready to apply the patch.
- You should apply only 1 SECUADO patch to 1 application site every 24 hours. The patch should only be worn for 24 hours. Do not wear the patch longer than 24 hours.
- Avoid bathing or swimming while wearing the patch. Swimming or bathing may cause the patch to fall off. You may shower.
- Avoid exposing the patch application site to direct heat sources such as hair dryers, heating pads, electric blankets, or heated water beds.
- If your skin feels irritated or feels like it is burning after you apply the patch, remove the patch and apply a new patch to a new application site.

Applying your SECUADO patch:

- Change (rotate) your patch application site every time you apply a new patch. Changing your application site every time you apply a patch will help to lessen your chances of developing skin irritation at the application site. Do not use the same application site 2 times in a row.
- The application site you choose should be clean, dry, and intact. Do not apply the patch on skin that has cuts, scrapes, burns, rashes, redness, or other skin problems.
- The application site you choose should be hairless or nearly hairless. If there is a lot of hair, use scissors to clip the hair as close to the skin as possible. Do not shave the application site.
- Do not apply the patch on skin that has oils, lotions, or powders on it.
- Do not apply the patch to areas of your skin where you wear tight clothing, such as waistbands, bras, or tank top straps.

Step 1.

- Always remove the used patch before applying a new one. You should only wear 1 patch at a time.
- Choose 1 application site to apply 1 patch.
- The application site you may choose should be one of the approved sites listed. Apply the patch to the left or right:
  - upper arm
  - upper back
  - stomach area (abdomen)
  - hip

Step 2.
When you are ready to apply your patch, use scissors and carefully cut the protective pouch along the dashed line to open the pouch and remove the patch. Do not cut the SECUADO patch.

- Do not use the patch if it is cut or damaged or if the seal on the pouch is broken. Throw it away and get a new one.

- Apply the patch right away after removing it from the pouch.

Step 3.
Hold the patch with the protective liner facing you. Bend the patch along the wave-shaped line in the middle of the protective liner. Slowly peel half of the protective liner off your patch.

- Do not touch the sticky side of the patch.

Step 4.
Holding the other half of the protective liner, apply the sticky half of the patch to the application site you chose and smooth it down with your fingers.

Step 5.
Hold the edge of the remaining half of the protective liner, then slowly peel it away and smooth the patch down onto your skin with your fingers.

Step 6.
Press and hold the patch firmly with the palm of your hand to make sure the patch and edges are sticking to your skin.

- Check the patch regularly during the day to make sure the patch is still firmly attached to your skin, especially after showering, using the bathroom, undressing, changing clothes, sleeping, or sweating.

- If the patch edges lift off your skin, you should smooth down edges with your fingers, press and hold the patch firmly with the palm of your hand.

- If your patch falls off, do not reapply the same patch. Choose a new application site, and repeat Steps 1 through 7 to apply a new SECUADO patch. Then, follow your normal schedule for changing the patch.

Step 7.
Wash your hands with soap and water after applying the patch.

Removing and disposing of your used SECUADO patch:

Step 8.
After you have worn the patch for 24 hours, remove the used patch from your skin and fold it in half so that the sticky sides stick together.

- Your used patch still has some medicine and should be folded.

- If the patch is hard to remove from the skin, gently apply an oil-based product (petroleum jelly, olive oil, or mineral oil) to the patch edges.

- If any adhesive (glue) remains on the skin after you remove the patch, apply an oil-based product or lotion to help with the removal.

Step 9.
Safely throw away the used folded patch in the trash right away so that children and pets cannot reach it

Step 10.
Wash your hands with soap and water after removing the patch.

How should I store SECUADO patch?

- Store SECUADO patches at room temperature between 68°F to 77°F (20°C to 25°C).
- Keep SECUADO patches and all medicines out of the reach of children.

Manufactured by: Hisamitsu Pharmaceutical Co., Inc., 408, Tashirodaikan-machi, Tosu, Saga, Japan ©2019-2023, Hisamitsu Pharmaceutical Co., Inc. All rights reserved.

Distributed by: Noven Therapeutics, LLC, Miami, Florida USA

SECUADO is a registered trademark of Hisamitsu Pharmaceutical Co., Inc.

This Instructions for Use has been approved by the U.S. Food and Drug Administration.

4O134A-0

Revised: 12/2023

PRINCIPAL DISPLAY PANEL - NDC: 68968-0172-3 - Carton Label - 3.8 mg/24 hours

NDC 68968-0172-3

PUSH IN

PULL UP

Secuado®

(asenapien)

transdermal system

3.8 mg/24 hours

For Transdermal Use Only

30 Transdermal Systems

Rx only

Each 20cm^2 system contains 6.4mg asenapine.

Inactive ingredients: Alicylic saturated hydrocarbon resin, butylated hydroxytoluene, isopropyl palmitate, maleate salts (monosodium maleate and disodium maleate), mineral oil, polyester film backing, polyisobutylene, silicone-treated polyester release liner, sodium acetate anhydrous, and styrene-isoprene-styrene block copolymer.

Dosage and Administration: See package insert.

Important: Read Instructions for Use for application and proper use. Do not wear more than one Secuado transdermal system at a time. Apply immediately upon removal from pouch. To dispose, fold used transdermal system in half (sticky sides together) and place in trash right away.
Keep out of the reach of children.

Do not store unpouched. Store at room temperature at 20°C to 25°C (68°F to 77°F).

Find out more at www.secuado.com

1M418T-0

Manufactured by

Hisamitsu Pharmaceutical Co., Inc.

408, Tashirodaikan-machi, Tosu, Saga, Japan

Distributed by

Noven Therapeutics, LLC

Miami, FL 33186

PRINCIPAL DISPLAY PANEL - NDC: 68968-0173-3 - Carton Label - 5.7 mg/24 hours

NDC 68968-0173-3

PUSH IN

PULL UP

Secuado®

(asenapien)

transdermal system

5.7 mg/24 hours

For Transdermal Use Only

30 Transdermal Systems

Rx only

Each 30cm^2 system contains 9.6mg asenapine.

Inactive ingredients: Alicylic saturated hydrocarbon resin, butylated hydroxytoluene, isopropyl palmitate, maleate salts (monosodium maleate and disodium maleate), mineral oil, polyester film backing, polyisobutylene, silicone-treated polyester release liner, sodium acetate anhydrous, and styrene-isoprene-styrene block copolymer.

Dosage and Administration: See package insert.

Important: Read Instructions for Use for application and proper use. Do not wear more than one Secuado transdermal system at a time. Apply immediately upon removal from pouch. To dispose, fold used transdermal system in half (sticky sides together) and place in trash right away.
Keep out of the reach of children.

Do not store unpouched. Store at room temperature at 20°C to 25°C (68°F to 77°F).

Find out more at www.secuado.com

1M419T-0

Manufactured by

Hisamitsu Pharmaceutical Co., Inc.

408, Tashirodaikan-machi, Tosu, Saga, Japan

Distributed by

Noven Therapeutics, LLC

Miami, FL 33186

PRINCIPAL DISPLAY PANEL - NDC: 68968-0174-3 - Carton Label - 7.6 mg/24 hours

NDC 68968-0174-3

PUSH IN

PULL UP

Secuado®

(asenapien)

transdermal system

7.6 mg/24 hours

For Transdermal Use Only

30 Transdermal Systems

Rx only

Each 40cm^2 system contains 12.8mg asenapine.

Inactive ingredients: Alicylic saturated hydrocarbon resin, butylated hydroxytoluene, isopropyl palmitate, maleate salts (monosodium maleate and disodium maleate), mineral oil, polyester film backing, polyisobutylene, silicone-treated polyester release liner, sodium acetate anhydrous, and styrene-isoprene-styrene block copolymer.

Dosage and Administration: See package insert.

Important: Read Instructions for Use for application and proper use. Do not wear more than one Secuado transdermal system at a time. Apply immediately upon removal from pouch. To dispose, fold used transdermal system in half (sticky sides together) and place in trash right away.

Keep out of the reach of children.

Do not store unpouched. Store at room temperature at 20°C to 25°C (68°F to 77°F).

Find out more at www.secuado.com

1M420T-0

Manufactured by

Hisamitsu Pharmaceutical Co., Inc.

408, Tashirodaikan-machi, Tosu, Saga, Japan

Distributed by

Noven Therapeutics, LLC

Miami, FL 33186